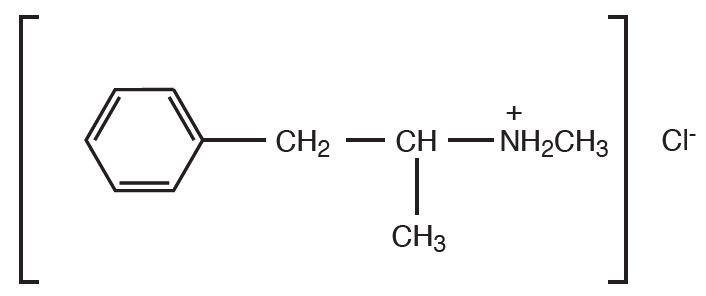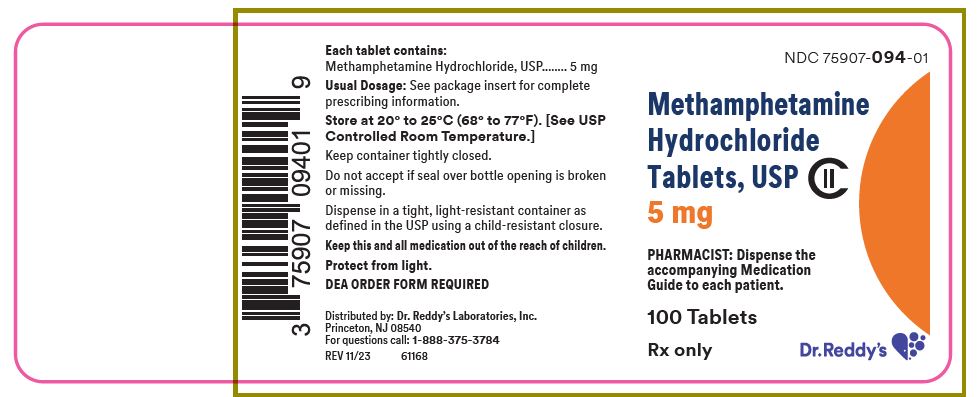 DRUG LABEL: Methamphetamine Hydrochloride
NDC: 75907-094 | Form: TABLET
Manufacturer: Dr. Reddy's Laboratories Inc
Category: prescription | Type: HUMAN PRESCRIPTION DRUG LABEL
Date: 20251107
DEA Schedule: CII

ACTIVE INGREDIENTS: METHAMPHETAMINE HYDROCHLORIDE 5 mg/1 1
INACTIVE INGREDIENTS: starch, corn; lactose monohydrate; stearic acid; talc

HIGHLIGHTS OF PRESCRIBING INFORMATION

These highlights do not include all the information needed to use METHAMPHETAMINE HYDROCHLORIDE TABLETS, USP safely and effectively. See full prescribing information for METHAMPHETAMINE HYDROCHLORIDE TABLETS, USP.
METHAMPHETAMINE HYDROCHLORIDE TABLETS, USP, for oral use, CII
Initial U.S. Approval: 1943

WARNING: ABUSE, MISUSE, AND ADDICTION

See full prescribing information for complete boxed warning.

METHAMPHETAMINE has a high potential for abuse and misuse, which can lead to the development of a substance use disorder, including addiction. Misuse and abuse of CNS stimulants, including METHAMPHETAMINE, can result in overdose and death. (5.1, 9.2, 10):

- Before prescribing METHAMPHETAMINE, assess each patient’s risk for abuse, misuse, and addiction.
- Educate patients and their families about these risks, proper storage of each drug, and proper disposal of any unused drug.
- Throughout treatment, reassess each patient’s risk and frequently monitor for signs and symptoms of abuse, misuse, and addiction.

1. INDICATIONS AND USAGE

Methamphetamine hydrochloride tablets, USP is a central nervous system (CNS) stimulant indicated for the treatment of Attention Deficit Hyperactivity Disorder (ADHD) in pediatric patients 6 years of age and older.

2. DOSAGE & ADMINISTRATION

- Administer methamphetamine hydrochloride tablets, USP orally once daily or in two divided doses daily. Avoid administration late in the evening due to the risk of insomnia. (2.2)
- Recommended starting dosage is 5 mg once or twice a daily. (2.3)
- Daily dosage may be increased in 5 mg increments at weekly intervals depending on clinical response. (2.3)
- The recommended dosage range is 20 mg to 25 mg daily. (2.3)

3. DOSAGE FORMS AND STRENGTHS

Tablets: 5 mg

4. CONTRAINDICATIONS

- Known hypersensitivity to amphetamine, or other components of methamphetamine hydrochloride tablets, USP. (4)
- Concomitant use of monoamine oxidase inhibitors (MAOIs), or use of an MAOI within the preceding 14 days. (4)

5. WARNINGS AND PRECAUTIONS

- Risks to Patients with Serious Cardiac Disease: Avoid use in patients with known structural cardiac abnormalities, cardiomyopathy, serious cardiac arrhythmias, coronary artery disease, or other serious cardiac disease. (5.2).
- Increased Blood Pressure and Heart Rate: Monitor blood pressure and pulse. (5.3)
- Psychiatric Adverse Reactions: Prior to initiating methamphetamine hydrochloride tablets, USP, screen patients for risk factors for developing a manic episode. If new psychotic or manic symptoms occur, consider discontinuing methamphetamine hydrochloride tablets, USP (5.4)
- Long-Term Suppression of Growth in Pediatric Patients: Closely monitor growth (height and weight) in pediatric patients. Pediatric patients not growing or gaining height or weight as expected may need to have their treatment interrupted. (5.5)
- Peripheral Vasculopathy, including Raynaud’s Phenomenon: Careful observation for digital changes is necessary during methamphetamine treatment. Further clinical evaluation (e.g., rheumatology referral) may be appropriate for patients who develop signs or symptoms of peripheral vasculopathy. (5.6)
- Seizures: May lower the convulsive threshold. If a seizure occurs, discontinue methamphetamine hydrochloride tablets, USP. (5.7)
- Serotonin Syndrome: Increased risk when coadministered with serotonergic agents (e.g., SSRIs, SNRIs, triptans), but also during overdosage situations. If it occurs, discontinue methamphetamine hydrochloride tablets, USP and initiate supportive treatment. (5.8)
- Motor and Verbal Tics, and Worsening of Tourette’s Syndrome: Before initiating methamphetamine hydrochloride tablets, USP, assess the family history and clinically evaluate patients for tics or Tourette’s syndrome. Regularly monitor patients for the emergence or worsening of tics or Tourette’s syndrome. Discontinue treatment if clinically appropriate. (5.9)

6. ADVERSE REACTIONS

Common adverse reactions include: palpitation, dizziness, insomnia, tremor, headache, diarrhea, dryness of mouth.

To report SUSPECTED ADVERSE REACTIONS, contact Dr. Reddy’s Laboratories at 1-888-375-3784 or FDA at 1-800-FDA-1088 or www.fda.gov/medwatch.

7. DRUG INTERACTIONS

Acidifying and Alkalinizing Agents: Agents that alter GI and urinary pH can alter blood levels of amphetamine. Acidifying agents can decrease amphetamine blood levels, while alkalinizing agents can increase amphetamine blood levels. (7.1)

8. USE IN SPECIFIC POPULATIONS

- Pregnancy: May cause fetal harm. (8.1)
- Lactation: Breastfeeding not recommended. (8.2)

FULL PRESCRIBING INFORMATION

WARNING: ABUSE, MISUSE, AND ADDICTION

METHAMPHETAMINE has a high potential for abuse and misuse, which can lead to the development of a substance use disorder, including addiction. Misuse and abuse of CNS stimulants, including METHAMPHETAMINE, can result in overdose and death [see Overdosage (10)], and this risk is increased with higher doses or unapproved methods of administration, such as snorting or injection.

Before prescribing METHAMPHETAMINE, assess each patient’s risk for abuse, misuse, and addiction. Educate patients and their families about these risks, proper storage of the drug, and proper disposal of any unused drug. Throughout METHAMPHETAMINE treatment, reassess each patient’s risk of abuse, misuse, and addiction and frequently monitor for signs and symptoms of abuse, misuse, and addiction [see Warnings and Precautions (5.1) and Drug Abuse and Dependence (9.2)].

1. INDICATIONS AND USAGE

Methamphetamine hydrochloride tablets, USP is indicated for the treatment of Attention Deficit Hyperactivity Disorder (ADHD) in pediatric patients 6 years of age and older.

2. DOSAGE & ADMINISTRATION

2.1 Pretreatment Screening

Prior to treating patients with methamphetamine hydrochloride tablets, USP, assess:

- for the presence of cardiac disease (i.e., perform a careful history, family history of sudden death or ventricular arrhythmia, and physical examination) [see Warnings and Precautions (5.2)].
- the family history and clinically evaluate patients for motor or verbal tics or Tourette’s syndrome before initiating methamphetamine hydrochloride tablets, USP [see WARNINGS AND PRECAUTIONS (5.9)].

2.2 Important Dosing Information

Administer methamphetamine hydrochloride tablets, USP orally once daily or in two divided doses daily. Avoid taking methamphetamine hydrochloride tablets, USP late in the evening due to the risk of insomnia.

2.3 Recommended Dosage

For pediatric patients 6 years of age and older, the recommended starting dosage is 5 mg methamphetamine hydrochloride tablets, USP once or twice daily. The daily dosage may be increased in increments of 5 mg at weekly intervals based on clinical response of the patient. The recommended dosage range is 20 mg to 25 mg daily.

2.4 Dosage Modifications Due to Drug Interactions

Agents that alter urinary pH can impact excretion and alter blood levels of amphetamine. Acidifying agents (e.g., ascorbic acid) decrease blood levels, while alkalinizing agents (e.g., sodium bicarbonate) increase blood levels. Adjust methamphetamine dosage based on clinical response [see Drug Interactions (7.1)].

3. DOSAGE FORMS AND STRENGTHS

Tablets: 5 mg of methamphetamine hydrochloride as white, round, unscored tablets debossed with 115 on one side of the tablet and blank on the other side.

4. CONTRAINDICATIONS

Methamphetamine hydrochloride tablets, USP is contraindicated in patients with:

- known hypersensitivity to amphetamine, or other components of methamphetamine. Hypersensitivity reactions such as angioedema and anaphylactic reactions have been reported in patients treated with other amphetamine products [see Adverse Reactions (6)].
- taking monoamine oxidase inhibitors (MAOIs), or within 14 days following discontinuation of treatment with an MAOIs (including MAOIs such as linezolid or intravenous methylene blue), because of the risk of hypertensive crisis [see Drug Interactions (7.1)].

5. WARNINGS AND PRECAUTIONS

5.1 Abuse, Misuse, and Addiction

Methamphetamine has a high potential for abuse and misuse. The use of methamphetamine exposes individuals to the risks of abuse and misuse, which can lead to the development of a substance use disorder, including addiction. Methamphetamine can be diverted for non-medical use into illicit channels or distribution [see Drug Abuse and Dependence (9.2, 9.3)]. Misuse and abuse of CNS stimulants, including methamphetamine, can result in overdose and death [see Overdosage (10)], and this risk is increased with higher doses or unapproved methods of administration, such as snorting or injection.

Before prescribing methamphetamine, assess each patient’s risk for abuse, misuse, and addiction. Educate patients and their families about these risks and proper disposal of any unused drug. Advise patients to store methamphetamine in a safe place, preferably locked, and instruct patients to not give methamphetamine to anyone else. Throughout methamphetamine treatment, reassess each patient’s risk of abuse, misuse, and addiction and frequently monitor for signs and symptoms of abuse, misuse, and addiction.

5.2 Risks to Patients with Serious Cardiac Disease

Sudden death has been reported in patients with structural cardiac abnormalities and other serious cardiac disease who were treated with CNS stimulants at recommended ADHD dosage.

Avoid methamphetamine use in patients with known structural cardiac abnormalities, cardiomyopathy, serious heart arrhythmia, coronary artery disease, and other serious heart problems.

5.3 Increased Blood Pressure and Heart Rate

CNS stimulants cause an increase in blood pressure (mean increase about 2 to 4 mm Hg) and heart rate (mean increase about 3 to 6 bpm). Some patients may have larger increases.

Monitor all methamphetamine-treated patients for potential tachycardia and hypertension [see Adverse Reactions (6)].

5.4 Psychiatric Adverse Reactions

Exacerbation of Pre-Existing Psychosis

CNS stimulants may exacerbate symptoms of behavior disturbance and thought disorder in patients with a pre-existing psychotic disorder.

Induction of a Manic Episode in Patients with Bipolar Illness

CNS stimulants may induce a mixed or manic episode in patients with bipolar disorder. Prior to initiating methamphetamine treatment, screen patients for risk factors for developing a manic episode (e.g., comorbid or has a history of depressive symptoms or a family history of suicide, bipolar disorder, and depression).

New Psychotic or Manic Symptoms

CNS stimulants, at recommended doses, may cause psychotic or manic symptoms (e.g., hallucinations, delusional thinking, or mania) in patients without prior history of psychotic illness or mania. In a pooled analysis of multiple short-term, placebo-controlled studies of CNS stimulants, psychotic or manic symptoms occurred in 0.1% of CNS stimulant-treated patients compared to 0% in placebo-treated patients. If such symptoms occur, consider discontinuing methamphetamine.

5.5 Long-Term Suppression of Growth in Pediatric Patients

CNS stimulants have been associated with weight loss and slowing of growth rate in pediatric patients. Closely monitor growth (weight and height) in methamphetamine-treated pediatric patients treated with CNS stimulants.

Pediatric patients who are not growing or gaining height or weight as expected may need to have their treatment interrupted.

5.6 Peripheral Vasculopathy, including Raynaud’s Phenomenon

CNS stimulants, including methamphetamine, used to treat ADHD are associated with peripheralvasculopathy, including Raynaud’s phenomenon. Signs and symptoms are usually intermittent and mild; however, very rare sequelae include digital ulceration and/or soft tissue breakdown. Effects of peripheral vasculopathy, including Raynaud’s phenomenon, were observed in post- marketing reports at different times and at therapeutic doses in all age groups throughout the course of treatment. Signs and symptoms generally improve after reduction in dose or discontinuation of CNS stimulant.

Careful observation for digital changes is necessary during methamphetamine treatment. Further clinical evaluation (e.g., rheumatology referral) may be appropriate for methamphetamine-treated patients who develop signs or symptoms of peripheral vasculopathy.

5.7 Seizures

Methamphetamine may lower the convulsive threshold in patients with prior history of seizure, in patients with prior EEG abnormalities in the absence of seizures, and in patients without a history of seizures and no prior EEG evidence of seizures. In the presence of seizures, methamphetamine should be discontinued.

5.8 Serotonin Syndrome

Serotonin syndrome, a potentially life-threatening reaction, may occur when amphetamines are used in combination with other drugs that affect the serotonergic neurotransmitter systems such as monoamine oxidase inhibitors (MAOIs), selective serotonin reuptake inhibitors (SSRIs), serotonin norepinephrine reuptake inhibitors (SNRIs), triptans, tricyclic antidepressants, fentanyl, lithium, tramadol, tryptophan, buspirone, and St. John’s Wort [see Drug Interactions (7.1)]. The coadministration with cytochrome P450 2D6 (CYP2D6) inhibitors may also increase the risk with increased exposure to methamphetamine. In these situations, consider an alternative nonserotonergic drug or an alternative drug that does not inhibit CYP2D6 [see Drug Interactions (7.1)].

Serotonin syndrome symptoms may include mental status changes (e.g., agitation, hallucinations, delirium, and coma), autonomic instability (e.g., tachycardia, labile blood pressure, dizziness, diaphoresis, flushing, hyperthermia), neuromuscular symptoms (e.g., tremor, rigidity, myoclonus, hyperreflexia, incoordination), seizures, and/or gastrointestinal symptoms (e.g., nausea, vomiting, diarrhea).

Concomitant use of methamphetamine with MAOI drugs is contraindicated [see Contraindications (4)].

Discontinue treatment with methamphetamine and any concomitant serotonergic agents immediately if the above symptoms occur, and initiate supportive symptomatic treatment. If concomitant use of methamphetamine with other serotonergic drugs or CYP2D6 inhibitors is clinically warranted, initiate methamphetamine with lower doses, monitor patients for the emergence of serotonin syndrome during drug initiation or titration, and inform patients of the increased risk for serotonin syndrome.

5.9 Motor and Verbal Tics, and Worsening of Tourette’s Syndrome

CNS stimulants, including amphetamine, have been associated with the onset or exacerbation of motor and verbal tics. Worsening of Tourette’s syndrome has also been reported [see Adverse Reactions (6)].

Before initiating methamphetamine, assess the family history and clinically evaluate patients for tics or Tourette’s syndrome. Regularly monitor methamphetamine-treated patients for the emergence orworsening of tics or Tourette’s syndrome, and discontinue treatment if clinically appropriate.

6. ADVERSE REACTIONS

The following adverse reactions are discussed in greater detail in other sections of the labeling:

- Abuse, Misuse, and Addiction[see Boxed Warning, Warnings and Precautions (5.1), Drug Abuse and Dependence (9.2, 9.3)]
- Hypersensitivity to amphetamine products or other ingredients of methamphetamine [see Contraindications (4)]
- Hypertensive Crisis When Used Concomitantly with Monoamine Oxidase Inhibitors [see Contraindications (4), Drug Interactions (7.1)]
- Risks to Patient with Serious Cardiac Disease [see Warnings and Precautions (5.2)]
- Increased Blood Pressure and Heart Rate [see Warnings and Precautions (5.3)]
- Psychiatric Adverse Reactions [see Warnings and Precautions (5.4)]
- Long-Term Suppression of Growth in Pediatric Patients[see Warnings and Precautions (5.5)]
- Peripheral Vasculopathy, including Raynaud’s Phenomenon [see Warnings and Precautions (5.6)]
- Seizures [see Warnings and Precautions (5.7)]
- Serotonin Syndrome [see Warnings and Precautions (5.8)]
- Motor and Verbal Tics, and Worsening of Tourette’s Syndrome[see Warnings and Precautions (5.9)]

The following adverse reactions associated with the use of methamphetamine were identified in clinical trials or postmarketing reports. Because these reactions were reported voluntarily from a population of uncertain size, it is not always possible to reliably estimate their frequency or establish a causal relationship to drug exposure.

Cardiovascular: Elevation of blood pressure, tachycardia and palpitation. Fatal cardiorespiratory arrest has been reported, mostly in the context of abuse/misuse

Central Nervous System: Psychotic episodes reported at recommended doses. Dizziness, dysphoria, overstimulation, euphoria, insomnia, tremor, restlessness and headache. Exacerbation of motor and verbal tics and Tourette’s syndrome

Gastrointestinal: Diarrhea, constipation, dryness of mouth, unpleasant taste, intestinal ischemia, and other gastrointestinal disturbances

Hypersensitivity: Urticaria

Endocrine: Impotence and changes in libido; frequent or prolonged erections

Musculoskeletal: Rhabdomyolysis

Metabolism and Nutrition Disorders: Suppression of growth has been reported with the long- term use of stimulants in pediatric patients

Skin and Subcutaneous Tissue Disorders: Alopecia

The following additional adverse reactions have been identified during post approval use of amphetamines:

Allergic: Rash, hypersensitivity reactions, including angioedema and anaphylaxis. Serious skin rashes, including Stevens-Johnson syndrome and toxic epidermal necrolysis have been reported.

Cardiovascular: Dyspnea, sudden death, myocardial infarction. There have been isolated reports of cardiomyopathy associated with chronic amphetamine use

Central Nervous System: dyskinesia, fatigue, aggression, anger, logorrhea, dermatillomania, and paresthesia (including formication)

Eye Disorders: Mydriasis

Vascular Disorders: Raynaud’s phenomenon

7. DRUG INTERACTIONS

7.1 Drugs Having Clinically Important Interactions with methamphetamine hydrochloride tablets, USP

Table 1 presents clinically important drug interactions with methamphetamine hydrochloride tablets, USP .

Table 1: Clinically Important Drug Interactions with methamphetamine hydrochloride tablets, USP

Monoamine Oxidase Inhibitors (MAOI)
Clinical Impact: | MAOI antidepressants slow amphetamine metabolism, increasing amphetamines effect on the release of norepinephrine and other monoamines from adrenergic nerve endings causing headaches and other signs of hypertensive crisis. Toxic neurological effects and malignant hyperpyrexia can occur, sometimes with fatal results.
Intervention: | Concomitant use of methamphetamine hydrochloride tablets, USP with monoamine oxidase inhibitors (MAOIs) or within 14 days after discontinuing MAOI treatment is contraindicated [see Contraindications (4)].
Serotonergic Drugs
Clinical Impact: | The concomitant use of amphetamines, including methamphetamine hydrochloride tablets, USP , and serotonergic drugs increases the risk of serotonin syndrome.
Intervention: | Initiate methamphetamine hydrochloride tablets, USP with lower doses and monitor patients for signs and symptoms of serotonin syndrome, particularly during methamphetamine hydrochloride tablets, USP initiation or dosage increase. If serotonin syndrome occurs, discontinue methamphetamine hydrochloride tablets, USP and the concomitant serotonergic drug(s) [see Warnings and Precautions 5.8].
AlkalinizingAgents
Clinical Impact: | Alkalinizing agents may increase exposure to amphetamines and potentiate the action of amphetamine.
Intervention | Avoid co-administration of methamphetamine hydrochloride tablets, USP and gastrointestinal and urinary alkalinizing agents.
Acidifying Agents
Clinical Impact: | Acidifying agents lower blood levels and efficacy of amphetamines.
Intervention | Increase dose of methamphetamine hydrochloride tablets, USP based on clinical response.
Tricyclic Antidepressants
Clinical Impact: | May enhance the activity of tricyclic or sympathomimetic agents causing sustained increases in the concentration of d-amphetamine in the brain; cardiovascular effects can be potentiated.
Intervention | Monitor frequently and adjust methamphetamine hydrochloride tablets, USP dose or use alternative therapy based on clinical response.
CYP2D6 Inhibitors
Clinical Impact: | Concomitant use of methamphetamine hydrochloride tablets, USP and CYP2D6 inhibitors may increase the exposure of methamphetamine hydrochloride tablets, USP compared to the use of the drug alone, and increase the risk of serotonin syndrome.
Intervention | Start with lower doses and monitor patients for signs and symptoms of serotonin syndrome particularly during methamphetamine hydrochloride tablets, USP initiation and after a dosage increase. If serotonin syndrome occurs, discontinue methamphetamine hydrochloride tablets, USP and the CYP2D6 inhibitor [see Warnings and Precautions 5.8].
Gastric pH Modulators
Clinical Impact: | Time to maximum concentration (Tmax) of amphetamine is decreased compared to when administered alone.
Intervention | Monitor patients for changes in clinical effect and use alternative therapy based on clinical response.
Guanethidine
Clinical Impact: | Methamphetamine may decrease the hypotensive effect ofguanethidine.
Intervention | Monitor patients and adjust therapy based on clinicalresponse.

Insulin requirements in diabetes mellitus may be altered in association with the use of methamphetamine and the concomitant dietary regimen.

7.2 Drug/Laboratory Test Interactions

Amphetamines can cause a significant elevation in plasma corticosteroid levels. This increase is greatest in the evening. Amphetamines may interfere with urinary steroid determinations.

8. USE IN SPECIFIC POPULATIONS

8.1 Pregnancy

Pregnancy Exposure Registry

There is a pregnancy exposure registry that monitors pregnancy outcomes in women exposed to ADHD medications, including methamphetamine hydrochloride tablets, USP , during pregnancy. Healthcare providers are encouraged to advise patients to register by contacting the National Pregnancy Registry for ADHD Medications at 1- 866-961-2388 or visiting online at www.womensmentalhealth.org/research/pregnancyregistry/adhd-medications/.

Risk Summary

Available data from epidemiologic studies and postmarketing reports on use of methamphetamine and amphetamine in pregnant women over decades of use have not identified a drug-associated risk of major birth defects or miscarriage. Neonates exposed to amphetamines in utero are at risk for withdrawal symptoms following delivery. Adverse pregnancy outcomes including premature delivery and low birth weight have been seen in infants born to mothers taking amphetamines during pregnancy (see Clinical Considerations).

In animals, administration of methamphetamine during organogenesis resulted in developmental toxicity, including neonatal death and fetal malformations, at doses equivalent to the maximum recommended human dose (MRHD) on a mg/m^2 basis. Oral administration of methamphetamine to rats during pregnancy, pregnancy and lactation, or lactation resulted in developmental toxicity in the offspring, including, neonatal mortality and delayed development, at a maternal dose similar to the MRHD on a mg/m^2 basis.

The background risk of major birth defects and miscarriage for the indicated population is unknown. All pregnancies have a risk of birth defect, loss, or other adverse outcomes. In the U.S. general population, the estimated background risk of birth defects and miscarriage in clinically recognized pregnancies is 2% to 4% and 15% to 20%, respectively.

Clinical Considerations

Fetal/Neonatal Adverse Reactions

CNS stimulants, such as methamphetamine hydrochloride tablets, USP , cause vasoconstriction and thereby decrease placental perfusion. In addition, amphetamines can stimulate uterine contractions, increasing the risk of premature delivery. Infants born to mothers taking amphetamines during pregnancy have an increased risk of premature delivery and low birth weight.

Monitor infants born to mothers taking methamphetamine for symptoms of withdrawal such as feeding difficulties, irritability, agitation, and excessive drowsiness.

Data

Animal Data

Based on published data, methamphetamine administration during the period of organogenesis caused malformations and pup mortality in mammals at doses equivalent to the maximum recommended human dose (MRHD) on a mg/m2 basis. Oral administration of methamphetamine (0, or 3.75 mg/kg) to pregnant rats during gestation, throughout gestation and lactation, or only during lactation resulted in an increase in neonatal pup mortality. Delayed somatic development (pinna unfolding and eye opening) and impairments in neurobehavioral development (righting reflex, incline plane test, and forelimb grip strength) were observed in the pups. The dose with adverse effects was equivalent to the MRHD of 25 mg on a mg/m^2 basis.

8.2 Lactation

Risk Summary

Based on limited case reports in the published literature, methamphetamine and its active metabolite, amphetamine, are present in human milk. There are no reports of adverse effects on the breastfed infant. Long-term neurodevelopmental effects on infants from amphetamine exposure are unknown. It is possible that large doses of amphetamine might interfere with milk production, especially in women whose lactation is not well established. Because of the potential for serious adverse reactions in nursing infants, advise patients that breastfeeding is not recommended during treatment with methamphetamine hydrochloride tablets, USP .

8.4 Pediatric Use

The safety and effectiveness of methamphetamine hydrochloride tablets, USP for the treatment of ADHD have been established in pediatric patients aged 6 years and older.

The safety and effectiveness of methamphetamine hydrochloride tablets, USP have not been established in pediatric patients younger than 6 years old.

Growth Suppression

Growth should be monitored during treatment with stimulants, including methamphetamine hydrochloride tablets, USP. Pediatric patients who are not growing or gaining weight as expected may need to have their treatment interrupted [see Warnings and Precautions (5.5), Adverse Reactions (6)].

8.5 Geriatric Use

Clinical studies of methamphetamine hydrochloride tablets, USP did not include sufficient numbers of subjects age 65 years and over to determine whether elderly subjects respond differently from younger subjects.

9. DRUG ABUSE AND DEPENDENCE

9.1 Controlled Substance

Methamphetamine hydrochloride tablets, USP contains methamphetamine hydrochloride, a Schedule II controlled substance.

9.2 Abuse

Methamphetamine has a high potential for abuse and misuse which can lead to the development of a substance use disorder, including addiction[see Warnings and Precautions (5.1)]. Methamphetamine can be diverted for non-medical use into illicit channels or distribution.

Abuse is the intentional non-therapeutic use of a drug, even once, to achieve a desired psychological or physiological effect. Misuse is the intentional use, for therapeutic purposes, of a drug by an individual in a way other than prescribed by a health care provider or for whom it was not prescribed. Drug addiction is a cluster of behavioral, cognitive, and physiological phenomena that may include a strong desire to take the drug, difficulties in controlling drug use (e.g., continuing drug use despite harmful consequences, giving a higher priority to drug use than other activities and obligations), and possible tolerance or physical dependence.

Misuse and abuse of methamphetamine may cause increased heart rate, respiratory rate, or blood pressure; sweating; dilated pupils; hyperactivity; restlessness; insomnia; decreased appetite; loss of coordination; tremors; flushed skin; vomiting; and/or abdominal pain. Anxiety, psychosis, hostility, aggression, and suicidal or homicidal ideation have also been observed with CNS stimulants abuse and/or misuse. Misuse and abuse of CNS stimulants, including Methamphetamine, can result in overdose and death [see Overdosage (10)], and this risk is increased with higher doses or unapproved methods of administration, such as snorting or injection.

9.3 Dependence

Physical Dependence

Methamphetamine may produce physical dependence. Physical dependence is a state that develops as a result of physiological adaptation in response to repeated drug use, manifested by withdrawal signs and symptoms after abrupt discontinuation or a significant dose reduction of a drug.

Withdrawal signs and symptoms after abrupt discontinuation or dose reduction following prolonged use of CNS stimulants including methamphetamine include dysphoric mood; depression; fatigue; vivid, unpleasant dreams; insomnia or hypersomnia; increased appetite; and psychomotor retardation or agitation.

Tolerance

Methamphetamine may produce tolerance. Tolerance is a physiological state characterized by a reduced response to a drug after repeated administration (i.e., a higher dose of a drug is required to produce the same effect that was once obtained at a lower dose).

10. OVERDOSAGE

Clinical Effects of Overdose

Overdose of CNS stimulants is characterized by the following sympathomimetic effects:

- Cardiovascular effects including tachyarrhythmias, and hypertension or hypotension. Vasospasm, myocardial infarction, or aortic dissection may precipitate sudden cardiac death. Takotsubo cardiomyopathy may develop.

- CNS effects including psychomotor agitation, confusion, and hallucinations. Serotonin syndrome, seizures, cerebral vascular accidents, and coma may occur.

- Life-threatening hyperthermia (temperatures greater than 104°F) and rhabdomyolysis may develop.

Overdose Management

Consider the possibility of multiple drug ingestion. D-amphetamine is not dialyzable.

Consider contacting the Poison Help line (1-800-222-1222) or a medical toxicologist for additional overdose management recommendations.

11. DESCRIPTION

Methamphetamine hydrochloride tablets, USP contain methamphetamine, a central nervous system stimulant, in the form of hydrochloride salt. Methamphetamine hydrochloride is chemically known as (S) N,α dimethylbenzeneethanamine hydrochloride with molecular formula of C10H15N.HCl and molecular weight of 185.73 g/mol It has the following structural formula:

Methamphetamine hydrochloride tablets, USP contain 5 mg of methamphetamine hydrochloride, USP for oral administration.

Inactive Ingredients:

Corn starch, lactose monohydrate, stearic acid and talc.

12. CLINICAL PHARMACOLOGY

12.1 Mechanism of Action

Amphetamines are non-catecholamine sympathomimetic amines with CNS stimulant activity. The exact mode of therapeutic action in the treatment of ADHD is not known.

12.2 Pharmacodynamics

Amphetamines block the reuptake of norepinephrine and dopamine into the presynaptic neuron and increase the release of these monoamines into the extraneuronal space.

12.3 Pharmacokinetics

Absorption

Methamphetamine is absorbed from the gastrointestinal tract.

Elimination

Metabolism

The primary site of metabolism is in the liver by aromatic hydroxylation, N-dealkylation and deamination. At least seven metabolites have been identified in the urine. The biological half-life has been reported in the range of 4 to 5 hours.

Excretion

Excretion occurs primarily in the urine and is dependent on urine pH. Alkaline urine will significantly increase the drug half-life. Approximately 62% of an oral dose is eliminated in the urine within the first 24 hours with about one-third as intact drug and the remainder as metabolites.

13. NONCLINICAL TOXICOLOGY

13.1 Carcinogenesis, Mutagenesis, Impairment of Fertility

Carcinogenicity and Mutagenesis

Carcinogenicity, mutagenic, or genotoxic potential of methamphetamine has not been fully characterized.

Impairment of Fertility

There have been no adequate studies performed in animals at current standards to evaluate the effect of methamphetamine treatment on fertility. However, published studies in mice and rats exposed to repeated daily dosing of methamphetamine report irregular estrous cycling and decreased ovarian reserve in females, and decreased sperm density, motility, and percent of sperm with normal morphology in males. The clinical significance of these findings is not clear.

16. HOW SUPPLIED /STORAGE AND HANDLING

How Supplied

Methamphetamine hydrochloride tablets, USP are available containing 5 mg of methamphetamine hydrochloride, USP.

The 5 mg tablets are white, round, unscored tablets debossed with 115 on one side of the tablet and blank on the other side. They are available as follows:

NDC 75907-094-01
bottles of 100 tablets

Storage and Handling

Store at 20º to 25ºC (68º to 77ºF). [See USP Controlled Room Temperature.]
Protect from light.

Dispense in a tight, light-resistant container as defined in the USP using a child-resistant closure.

17. PATIENT COUNSELING INFORMATION

Advise the patient to read the FDA-approved patient labeling (Medication Guide).

Abuse, Misuse, and Addiction

Educate patients and their families about the risks of abuse, misuse, and addiction of methamphetamine hydrochloride tablets, USP , which can lead to overdose and death, and proper disposal of any unused drug [see Warnings and Precautions (5.1), Drug Abuse and Dependence (9.2), Overdosage (10)]. Advise patients to store methamphetamine hydrochloride tablets, USP in a safe place, preferably locked, and instruct patients to not give methamphetamine hydrochloride tablets, USP to anyone else.

Risks to Patients with Serious Cardiac Disease

Advise patients that there are potential risks to patients with serious cardiac disease, including sudden death with methamphetamine hydrochloride tablets, USP use. Instruct patients to contact a healthcare provider immediately if they develop symptoms such as exertional chest pain, unexplained syncope, or other symptoms suggestive of cardiac disease [see Warnings and Precautions (5.2)].

Increased Blood Pressure and Heart Rate

Instruct patients that methamphetamine hydrochloride tablets, USP can cause elevations of their blood pressure and pulse rate and they should be monitored for such effects [see Warnings and Precautions (5.3)].

Psychiatric Adverse Risks

Advise patients that methamphetamine hydrochloride tablets, USP , at recommended doses, may cause psychotic or manic symptoms even in patients without prior history of psychotic symptoms or mania [see Warnings and Precautions (5.4)].

Long-Term Suppression of Growth in Pediatric Patients

Advise patients, family members, and caregivers that methamphetamine hydrochloride tablets, USP may cause slowing of growth including weight loss [see Warnings and Precautions (5.5)].

Circulation problems in fingers and toes (peripheral vasculopathy, including Raynaud’s phenomenon)

Instruct patients beginning treatment with methamphetamine hydrochloride tablets, USP about the risk of peripheral vasculopathy, including Raynaud’s Phenomenon, and associated signs and symptoms: fingers or toes may feel numb, cool, painful, and/or may change color from pale, to blue, to red. Instruct patients to report to their physician any new numbness, pain, skin color change, or sensitivity to temperature in fingers or toes. Instruct patients to call their physician immediately with any signs of unexplained wounds appearing on fingers or toes while taking methamphetamine hydrochloride tablets, USP . Further clinical evaluation (e.g., rheumatology referral) may be appropriate for certain patients [see Warnings and Precautions (5.6)].

Seizures

Caution patient that methamphetamine hydrochloride tablets, USP may lower the convulsive threshold. Advise patients to contact their healthcare provider immediately and to discontinue methamphetamine hydrochloride tablets, USP if a seizure occurs [see Warnings and Precautions (5.7)].

Serotonin Syndrome

Caution patients about the risk of serotonin syndrome with concomitant use of methamphetamine hydrochloride tablets, USP and other serotonergic drugs including SSRIs, SNRIs, triptans, tricyclic antidepressants, fentanyl,lithium, tramadol, tryptophan, buspirone, St. John’s Wort, and with drugs that impair metabolism of serotonin (in particular MAOIs, both those intended to treat psychiatric disorders and also others such as linezolid [see Contraindications (4), Warnings and Precautions (5.8) and Drug Interactions (7.1)]. Advise patients to contact their healthcare provider or report to the emergency room if they experience signs or symptoms of serotonin syndrome.

Motor and Verbal Tics, and Worsening of Tourette’s Syndrome

Advise patients that motor and verbal tics and worsening of Tourette’s syndrome may occur during treatment with methamphetamine hydrochloride tablets, USP . Instruct patients to notify their healthcare provider ifemergence of new tics or worsening of tics or Tourette’s syndrome occurs [see Warnings and Precautions (5.9)].

Concomitant Medications

Advise patients to notify their physicians if they are taking, or plan to take, any prescription or over-the-counter drugs because there is a potential for interactions [see Drug Interactions (7.1)].

Pregnancy

Advise patients that there is a pregnancy exposure registry that monitors pregnancy outcomes in women exposed to methamphetamine hydrochloride tablets, USP during pregnancy. Advise patients to notify their healthcare provider if they become pregnant or intend to become pregnant during treatment with methamphetamine hydrochloride tablets, USP . Advise patients of the potential fetal effects from the use of methamphetamine hydrochloride tablets, USP during pregnancy [see Use in Specific Populations (8.1)].

Lactation

Advise patients not to breastfeed if they are taking methamphetamine hydrochloride tablets, USP [see Use in Specific Populations (8.2)].

Distributed by:

Dr. Reddy’s Laboratories Inc.

Princeton, NJ08540

Rev. 10/2024

MEDICATION GUIDE

METHAMPHETAMINE HYDROCHLORIDE TABLETS, USP CII
(metham-fetă-mēn hīdrŏ-klōrīd)

5 mg

What is the most important information I should know about methamphetamine hydrochloride tablets?

Methamphetamine hydrochloride tablets may cause serious side effects, including:

- Abuse, misuse, and addiction. Methamphetamine hydrochloride tablets has a high chance for abuse and misuse and may lead to substance use problems, including addiction. Misuse and abuse of Methamphetamine hydrochloride tablets, other amphetamine containing medicines, and methylphenidate containing medicines, can lead to overdose and death. The risk of overdose and death is increased with higher doses of Methamphetamine hydrochloride tablets or when it is used in ways that are not approved, such as snorting or injection.
  - Your healthcare provider should check your child’s risk for abuse, misuse, and addiction before starting treatment with Methamphetamine hydrochloride tablets and will monitor your child during treatment.
  - Methamphetamine hydrochloride tablets may lead to physical dependence after prolonged use, even if taken as directed by your healthcare provider.
  - Do not give Methamphetamine Hydrochloride tablets to anyone else. See “What is Methamphetamine hydrochloride tablets?” for more information.
  - Keep Methamphetamine Hydrochloride tablets in a safe place and properly dispose of any unused medicine. See “How should I store Methamphetamine hydrochloride tablets?” for more information.
  - Tell your healthcare provider if your child has ever abused or been dependent on alcohol, prescription medicines, or street drugs.
- Risks for people with serious heart disease. Sudden death has happened in people whohave heart defects or other serious heart disease.

Your child’s healthcare provider should check your child carefully for heart problems before starting treatment with Methamphetamine hydrochloride tablets. Tell your child’s healthcare provider if your child has any heart problems, heart disease, or heart defects.

Call your child’s healthcare provider or go to the nearest hospital emergency room right away if your child has any signs of heart problems such as chest pain, shortness of breath, or fainting during treatment with Methamphetamine Hydrochloride tablets.

- Increased blood pressure and heart rate. Your child’s healthcare provider should check your child’s blood pressure and heart rate regularly during treatment with Methamphetamine hydrochloride tablets.

- Mental (Psychiatric) problems, inlcudin

-
  - new or worse behavior and thought problems
  - new orworse bipolarillness
  - newpsychoticsymptoms(suchashearingvoices or seeing orbelievingthingsthatarenot real) or new manic symptoms

Tell your doctor if you have or your child has numbness, pain, skin color change, or sensitivity to temperature in your fingers or toes.

Call your child’s healthcare provider right away if your child has any new or worsening mental symptoms or problems during treatment with Methamphetamine hydrochloride tablets, especially hearing voices, seeing or believing things that are not real, or new manic symptoms.

What are Methamphetamine hydrochloride tablets?

Methamphetamine hydrochloride tablets are a central nervous system (CNS) stimulant prescription medicine used for the treatment of Attention Deficit Hyperactivity Disorder (ADHD) in children 6 years to 17 years of age. Methamphetamine hydrochloride tablets may help increase attention and decrease impulsiveness and hyperactivity in people with ADHD.It is not known if Methamphetamine hydrochloride tablets is safe and effective in children under 6 years of age.

Methamphetamine hydrochloride tablets is a federally controlled substance (CII) because it contains methamphetamine that can be a target for people who abuse prescription medicines or street drugs. Keep Methamphetamine hydrochloride tablets in a safe place to protect it from theft. Never give your Methamphetamine hydrochloride tablets to anyone else because it may cause death or harm them. Selling or giving away Methamphetamine hydrochloride tablets may harm others and is against the law.

Do not take Methamphetamine hydrochloride tablets if your child is:

- allergic to amphetamine or any of the ingredients in Methamphetamine hydrochloride tablets. See the end of this Medication Guide for a complete list of ingredients in Methamphetamine hydrochloride tablets.
- taking, or has stopped taking within the past 14 days, a medicine used to treat depression called a monoamine oxidase inhibitor (MAOI).

Before taking Methamphetamine hydrochloride tablets, tell your child’s healthcare provider about all your child’s medical conditions, including if your child:

- has heart problems, heart disease, heart defects, or high blood pressure
- has mental problems including psychosis, mania, bipolar illness or depression, or a family history of suicide bipolar illness, or depression
- has circulation problems in fingers and toes
- has kidney problems
- have or had repeated movements or sounds (tics) or Tourette’s syndrome, or have a family history of tics or Tourette’s syndrome
- has pregnant or plans to become pregnant.It is not known if methamphetamine hydrochloride tabletswill harm the unborn baby.
  - There is a pregnancy registry for femles who are exposed to Methamphetamine hydrochloride tablets during pregnancy. The purpose of the registry is to collect information about the health of females exposed to Methamphetamine hydrochloride tablets and their baby. If your child becomes pregnant during treatment with Methamphetamine hydrochloride tablets, talk to your child’s healthcare provider about registering with the National Pregnancy Registry for Psychostimulants. You can register by calling 1-866-961- 2388 or by visiting online at https://womensmentalhealth.org/clinical-and- researchprograms/pregnancyregistry/othermedications/
- is breastfeeding or plans to breastfeed. Methamphetamine hydrochloride tablets passes into breast milk. Your child should not breastfeed during treatment with Methamphetamine hydrochloride tablets. Talk to your child’s healthcare provider about the best way to feed the baby during treatment with Methamphetamine hydrochloride tablets.

Tell your child’s healthcare provider about all of the medicines that your child takes including prescription and over-the-counter medicines, vitamins, and herbalsupplements.

Methamphetamine hydrochloride tablets and some medicines may interact with each other and cause serious side effects. Sometimes the doses of other medicines will need to be changed during treatment with Methamphetamine hydrochloride tablets. Your child’s healthcare provider will decide whether Methamphetamine hydrochloride tablets can be taken with other medicines.

Especially tell your child’s healthcare provider if your child takes:

- medicines used to treat migraine headaches known as triptans
- tricyclic antidepressants
- fentanyl
- lithium
- tramadol
- tryptophan
- buspirone
- St. John’s Wort
- medicines used to treat mood, anxiety, psychotic or thought disorders, including selective serotonin reuptake inhibitors (SSRIs) and serotonin norepinephrine reuptake inhibitors (SNRIs)

Ask your child’s healthcare provider if you are not sure if your child takes any of these medicines. Know the medicines your child takes. Keep a list of your child’s medicines with you to show your child’s healthcare provider and pharmacist. Do not start any new medicine during treatment with Methamphetamine hydrochloride tablets without talking to your child’s healthcare provider first.

How should Methamphetamine hydrochloride tablets be taken?

- Take Methamphetamine hydrochloride tablets exactly as prescribed.
- Your child’s healthcare provider may change the dose or have your child stop taking Methamphetamine hydrochloride tablets if needed.
- Methamphetamine hydrochloride tablets is usually taken 1 or 2 times each day. Avoid taking Methamphetamine late in the evening because it may cause sleep problems.

If your child takes too much Methamphetamine hydrochloride tablets, call your child’s healthcare provider or Poison Help line at 1-800-222-1222 or go to the nearest hospital emergency room right away.

What are possible side effects of Methamphetamine hydrochloride tablets? Methamphetamine hydrochloride tablets may cause serious side effects, including:

- See “What is the most important information I should know about Methamphetamine hydrochloride tablets?”
- Slowing of growth (height and weight) in children. Children should have their height and weight checked often during treatment with Methamphetamine hydrochloride tablets. Methamphetamine hydrochloride tablets treatment may be stopped if your child is not growing or gaining weight.
- Circulation problems in fingers and toes (peripheral vasculopathy, including Raynaud’s phenomenon). Signs and symptoms may include:
  - fingers or toes may feel numb, cool, painful
  - fingers or toes may change color from pale, to blue, to red

Tell your child’s healthcare provider if your child has numbness, pain, skin color change, or sensitivity to temperature in your fingers or toes or if your child has any signs of unexplained wounds appearing on fingers or toes during treatment with Methamphetamine hydrochloride tablets.

- Serotonin syndrome. This problem may happen when Methamphetamine hydrochloride tablets is taken with certain other medicines and may be life-threatening. Call your healthcare provider or go to the nearest hospital emergency room if you have any of the following symptoms of serotonin syndrome:
  - agitation, hallucinations, coma
  - changes in blood pressure
  - high body temperature
  - dizziness
  - sweating or fever
  - muscle stiffness or tightness
  - fast heartbeat
  - flushing
  - seizures
  - nausea, vomiting, diarrhea
  - loss of coordination
  - confusion
- New or worsening tics or worsening Tourette’s syndrome. Tell your healthcare provider if you or your child get any new or worsening tics or worsening Tourette’s syndrome during treatment with Methamphetamine hydrochloride tablets.

The most common side effects with Methamphetamine hydrochloride tablets include:

- fast heartbeat or heart beating harder than normal
- dizziness
- trouble sleeping
- shaking
- headache
- diarrhea
- dry mouth

These are not all the possible side effects of Methamphetamine hydrochloride tablets.

Call your child’s healthcare provider for medical advice about side effects. You may report side effects to FDA at 1-800-FDA-1088 or www.fda.gov/medwatch or Dr. Reddy’s Laboratories at 1-888-375-3784.

How should I store Methamphetamine hydrochloride tablets?

- Store Methamphetamine hydrochloride tablets at room temperature between 68°F to 77°F (20°C to -25°C).
- Store Methamphetamine hydrochloride tablets in a safe place like a locked cabinet. Protect from light.
- Dispose of remaining, unused, or expired Methamphetamine hydrochloride tablets by a medicine take-back program at a U.S. Drug Enforcement Administration (DEA) authorized collection site. If no take-back program or DEA authorized collector is available, mix Methamphetamine hydrochloride tablets with an undesirable, nontoxic substance such as dirt, cat litter, or used coffee grounds to make it less appealing to children and pets. Place the mixture in a container such as a sealed plastic bag and throw away Methamphetamine hydrochloride tablets in the household trash. Visit www.fda.gov/drugdisposal for additional information on disposal of unused medicines.

Keep Methamphetamine hydrochloride tablets and all medicines out of the reach of children.

General information about the safe and effective use of Methamphetamine hydrochloride tablets.

Medicines are sometimes prescribed for purposes other than those listed in a Medication Guide. Do not use Methamphetamine hydrochloride tablets for a condition for which it was not prescribed. Do not give Methamphetamine hydrochloride tablets to other people, even if they have the same symptoms that your child has. It may harm them and it is against the law.

You can ask your child’s pharmacist or healthcare provider for information about Methamphetamine hydrochloride tablets that is written for healthcare professionals.

What are the ingredients in Methamphetamine hydrochloride tablets?

Active Ingredient: methamphetamine hydrochloride, USP

Inactive Ingredients: corn starch, lactose monohydrate, stearic acid and talc

Distributed by:

Dr. Reddy’s laboratories Inc.

Princeton, NJ 08540

Rev. 10/2024

PRINCIPAL DISPLAY PANEL - 5 mg Tablet Bottle Label

NDC 75907-094-01

Methamphetamine
Hydrochloride
Tablets, USP

CII

5 mg

PHARMACIST: Dispense the
accompanying Medication Guide to
each patient.

Rx Only

100 Tablets

Dr. Reddy's Laboratories, Inc